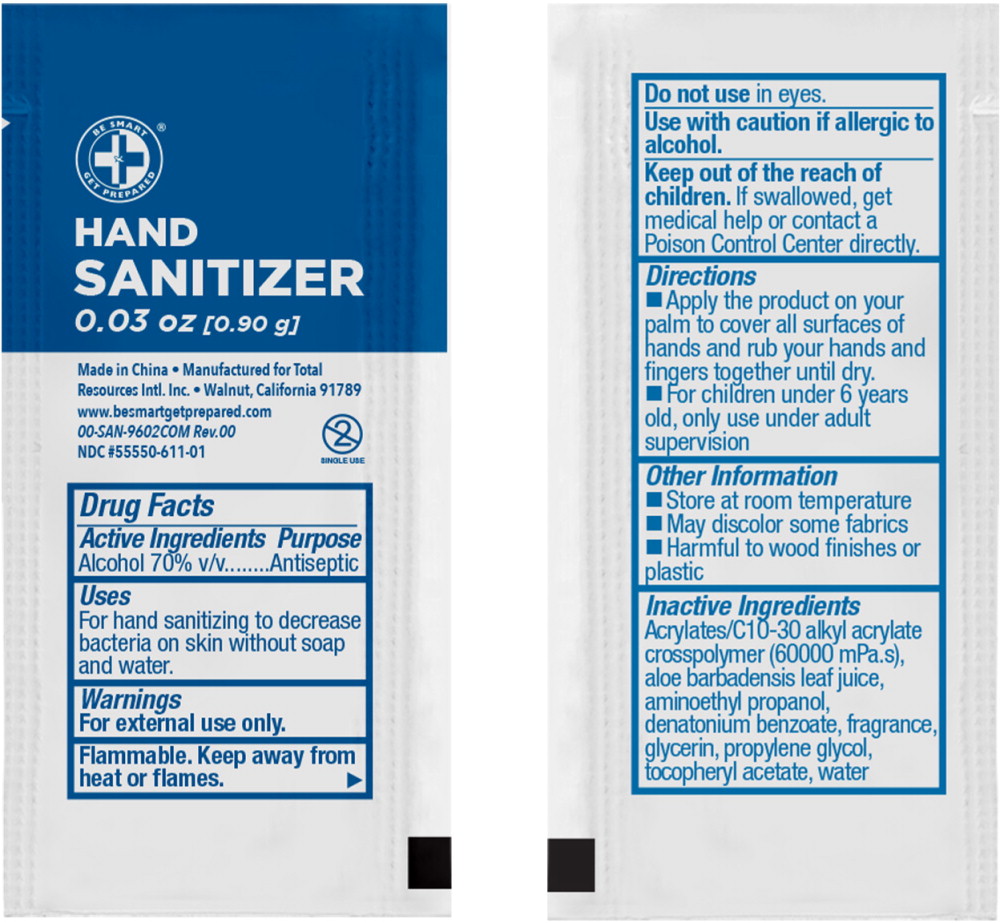 DRUG LABEL: Be Smart Get Prepared Hand Sanitizer
NDC: 55550-611 | Form: GEL
Manufacturer: Total Resources International, Inc
Category: otc | Type: HUMAN OTC DRUG LABEL
Date: 20240816

ACTIVE INGREDIENTS: ALCOHOL 0.700 mL/1 mL
INACTIVE INGREDIENTS: WATER; GLYCERIN; PROPYLENE GLYCOL; ACRYLATES/C10-30 ALKYL ACRYLATE CROSSPOLYMER (60000 MPA.S); AMINOMETHYLPROPANOL; ALOE VERA LEAF; .ALPHA.-TOCOPHEROL ACETATE; DENATONIUM BENZOATE

Drug Facts

Active Ingredients

Alcohol 70% v/v

Purpose

Antiseptic

Uses

For hand sanitizing to decrease bacteria on skin without soap and water

Warnings

For external use only.

Flammable. Keep away from heat or flames.

Do not use in eyes

Use with caution if allergic to alcohol.

Keep out of reach of children. If swallowed, get medical help or contact a Poison Control Center directly

Directions

- Apply the product on your palm to cover all surfaces of hands and rub your hands and fingers together until dry.
- For children under 6 years old, use under adult supervision

Other Information

- Store at room temperature
- May discolor some fabrics
- Harmful to wood finishes or plastic

Inactive Ingredients

Acrylates/C10-30 Alkyl Acrylate Crosspolymer (60000 mPa.s), aloe barbadensis leaf juice, aminoethyl propanol, denatonium benzoate, fragrance, glycerin, propylene glycol, tocopheryl acetate, water

Principal Display Panel – 1mL Pouch Label

BE SMART

GET PREPARED®

HAND SANITIZER

0.03 oz [0.90 g]

Single Use

Made in China

Manufactured for Total Resources Intl. Inc

Walnut, California 91789

www.besmartgetprepared.com • 00-SAN-9602COM Rev. 00

NDC 55550-611-01